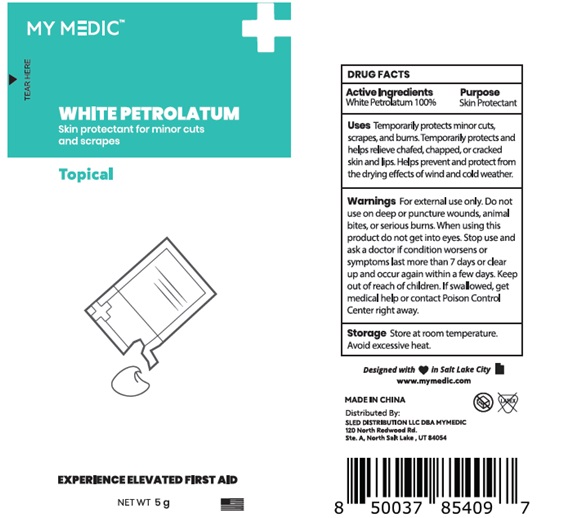 DRUG LABEL: White Petrolatum
NDC: 81417-004 | Form: CREAM
Manufacturer: Sled Distribution, LLC
Category: otc | Type: HUMAN OTC DRUG LABEL
Date: 20240115

ACTIVE INGREDIENTS: PETROLATUM 100 g/100 g
INACTIVE INGREDIENTS: WATER

81417-004 MY MEDIC WHITE PETROLATUM

Active ingredient

White petrolatum 100%

Purpose

Skin protectant

INDICATIONS AND USAGE

Uses Temporarily protects minor cuts, scrapes, and burns. Temporarily protects and helps relieve chafed, chapped, or cracked skin and lips. Helps prevent and protect from the drying effects of wind and cold weather.

Warnings

For External use only

Do not use on

- deep or puncture wounds
- animal bites
- or serious burns

When using this product do not get into eyes

Stop use and ask a doctor if

- condition worsens
- symptoms last more than 7 days or clear up and occur again in a few days

Keep out of reach of children.

If swallowed, get medical help or contact a Poison Control Center right away.

DOSAGE AND ADMINISTRATION

Directions apply as needed

Storage Store at room temperature. Avoid excessive heat.

INACTIVE INGREDIENT

water